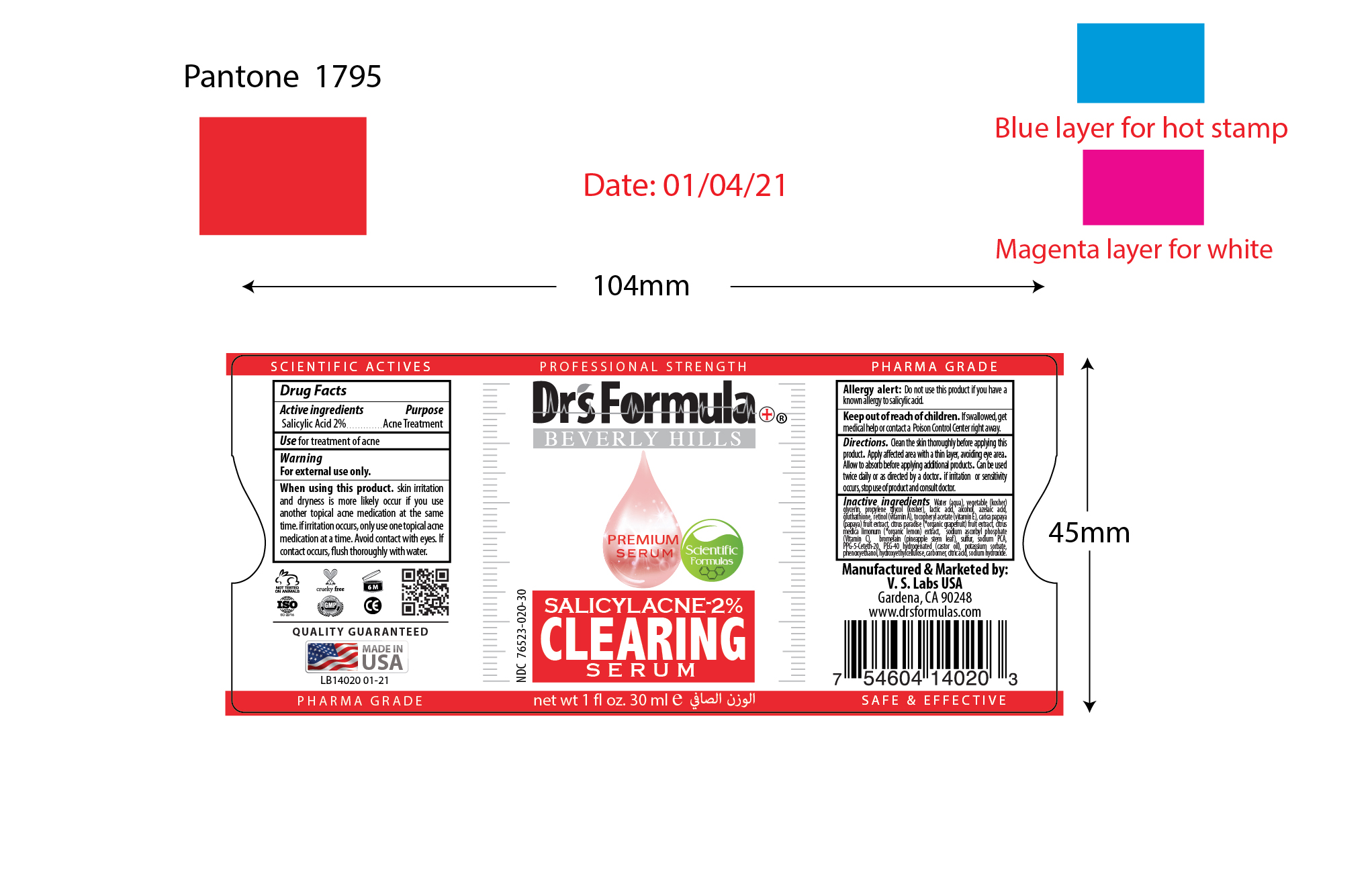 DRUG LABEL: Salicylacne-2% Clearing Serum
NDC: 76523-020 | Form: LIQUID
Manufacturer: Valley of the Sun Cosmetics LLC
Category: otc | Type: HUMAN OTC DRUG LABEL
Date: 20210616

ACTIVE INGREDIENTS: SALICYLIC ACID 2 g/100 mL
INACTIVE INGREDIENTS: ALCOHOL; VITAMIN A; LACTIC ACID; ASCORBIC ACID; CARICA PAPAYA WHOLE; CITRUS PARADISI WHOLE; STEM BROMELAIN; TECHNETIUM TC-99M SULFUR COLLOID; PPG-5-CETETH-20; PHENOXYETHANOL; CARBOMER 940; CITRIC ACID ACETATE; AZELAIC ACID; CITRUS MEDICA FRUIT; PEG-40 CASTOR OIL; POTASSIUM SORBATE; 1-PALMITOYL-2-OLEOYL-SN-GLYCERO-3-(PHOSPHO-RAC-(1-GLYCEROL)), SODIUM SALT; CETYL HYDROXYETHYLCELLULOSE (350000 MW); WATER; SODIUM HYDROXIDE; .ALPHA.-TOCOPHEROL ACETATE; GLYCERIN; 3-HEXYLOXYPROPYLENE GLYCOL; GLUTATHIONE

Salicylacne-2% Clearing Serum

Active Ingredients

Salicylic Acid 2%

Purpose

Acne Treatment

Uses

Use for treatment of acne

Warning

For external use only

Do not use

Allergy Alert: Do not use this product if you have a known allergy to salicylic acid.

When using this product

Skin irritation and dryness is more likely occur if you use another topical acne medication at the same time. If irritation occurs, only use one topical acne medication at a time. Avoid contact with eyes. If contact occurs, flush thoroughly with water.

Stop use and ask doctor

If irritation or sensitivity occurs, stop use of product and consult doctor.

Keep out of reach of children

If swallowed, get medical help or contact a Poison Control Center right away.

Directions

Clean the skin thoroughly before applying this product. Apply affected area with a thin layer, avoiding eye area. Allow to absorb before applying additional products. Can be used twice daily or as directed by a doctor.

Inactive ingredients

Water (aqua), vegetable (kosher) glycerin, propylene glycol (kosher), alcohol, retinol (vitamin A), tocopheryl acetate (vitamin E), azelaic acid, gluthathione, lactic acid, sodium ascorbyl phosphate (Vitamin C), carica papaya (papaya) fruit extract, citrus paradise (*organic grapefruit) fruit extract, citrus medica limonum (*organic lemon) extract, bromelain (*pineapple stem leaf), sulfur, sodium PCA, PPG-5-Ceteth-20, PEG-40 hydrogenated (castor oil), potassium sorbate, phenoxyethanol, hydroxyethylcellulose, carbomer, citric acid, sodium hydroxide